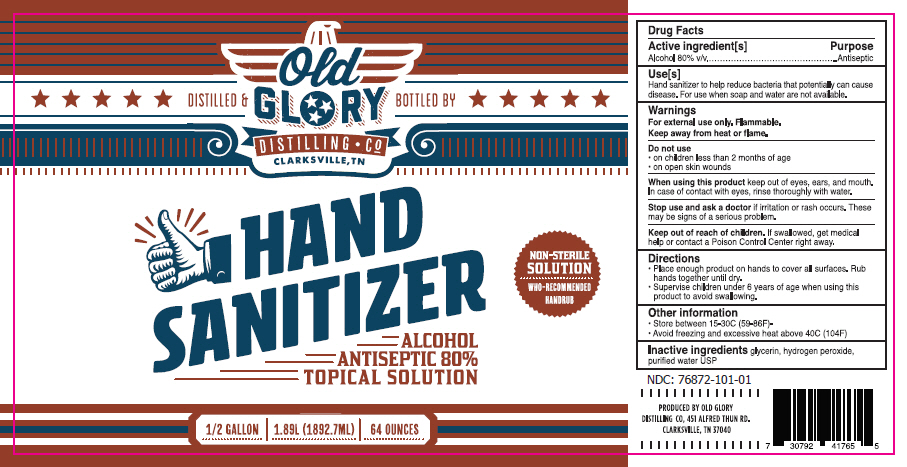 DRUG LABEL: HAND SANITIZER
NDC: 76872-101 | Form: LIQUID
Manufacturer: CUNNINGHAM SPIRITS LLC dba OLD GLORY DISTILLING CO.
Category: otc | Type: HUMAN OTC DRUG LABEL
Date: 20200519

ACTIVE INGREDIENTS: Alcohol 80 mL/100 mL
INACTIVE INGREDIENTS: glycerin; hydrogen peroxide; water

HAND SANITIZER

Drug Facts

Active ingredient[s]

Alcohol 80% v/v

Purpose

Antiseptic

Use[s]

Hand sanitizer to help reduce bacteria that potentially can cause disease. For use when soap and water are not available.

Warnings

For external use only. Flammable.

Keep away from heat or flame.

Do not use

- on children less than 2 months of age
- on open skin wounds

When using this product keep out of eyes, ears, and mouth. In case of contact with eyes, rinse thoroughly with water.

Stop use and ask a doctor if irritation or rash occurs. These may be signs of a serious problem.

Keep out of reach of children. If swallowed, get medical help or contact a Poison Control Center right away.

Directions

- Place enough product on hands to cover all surfaces. Rub hands together until dry.
- Supervise children under 6 years of age when using this product to avoid swallowing.

Other information

- Store between 15-30C (59-86F)-
- Avoid freezing and excessive heat above 40C (104F)

Inactive ingredients

glycerin, hydrogen peroxide, purified water USP

PRINCIPAL DISPLAY PANEL - 1892.7 ML Bottle Label

DISTILLED & BOTTLED BY
Old
GLORY
DISTILLING • Co
CLARKSVILLE, TN

HAND
SANITIZER
ALCOHOL
ANTISEPTIC 80%
TOPICAL SOLUTION

NON-STERILE
SOLUTION
WHO-RECOMMENDED
HANDRUB

1/2 GALLON | 1.89L (1892.7ML) | 64 OUNCES